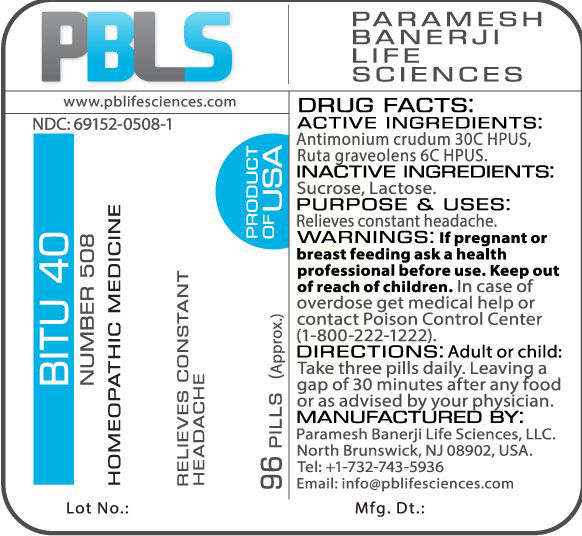 DRUG LABEL: Bitu 40 (Number 508)
NDC: 69152-0508 | Form: PELLET
Manufacturer: Paramesh Banerji Life Sciences LLC
Category: homeopathic | Type: HUMAN OTC DRUG LABEL
Date: 20170601

ACTIVE INGREDIENTS: ANTIMONY TRISULFIDE 30 [hp_C]/1 1; RUTA GRAVEOLENS FLOWERING TOP 6 [hp_C]/1 1
INACTIVE INGREDIENTS: SUCROSE; LACTOSE

DRUG FACTS: Active Ingredients

Antimonium crudum 30C HPUS, Ruta graveolens 6C HPUS

Inactive Ingredients

Sucrose, Lactose

Purpose

Relieves constant headache

Uses

Relieves constant headache

Warnings

If pregnant or breast feeding ask a health professional before use.

Keep out of reach of children. In case of overdose, get medical help or contact a Poison Control Center (1-800-222-1222) right away.

Direction

Adult or child: Take three pills daily. Leaving a gap of 30 minutes after any food or as advised by your physician.

Manufactured by

Paramesh Banerji Life Sciences, LLC.

North Brunswick, NJ 08902, USA.

Tel: +1-732-743-5936

Email: info@pblifesciences.com

Principal Display Panel

NDC: 69152-0508

Bitu 40

Number 508

Homeopathic Medicine

Relieves constant headache

96 Pills (Approx.)

Product of USA